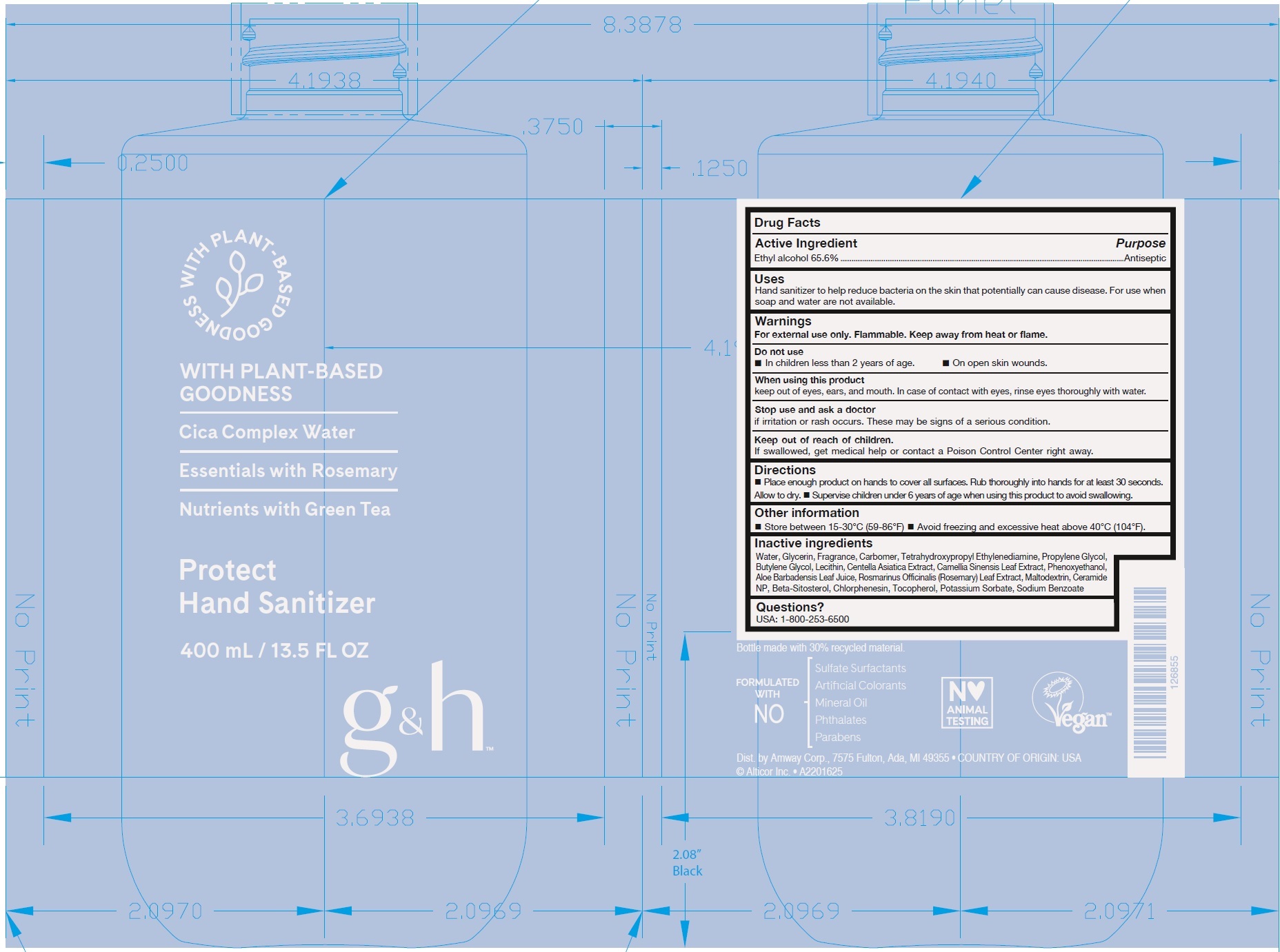 DRUG LABEL: G and H Protect Hand Sanitizer
NDC: 10056-532 | Form: GEL
Manufacturer: Access Business Group LLC
Category: otc | Type: HUMAN OTC DRUG LABEL
Date: 20231023

ACTIVE INGREDIENTS: ALCOHOL 65.6 mL/100 mL
INACTIVE INGREDIENTS: WATER; GLYCERIN; CARBOMER HOMOPOLYMER, UNSPECIFIED TYPE; EDETOL; PROPYLENE GLYCOL; BUTYLENE GLYCOL; CENTELLA ASIATICA TRITERPENOIDS; GREEN TEA LEAF; PHENOXYETHANOL; ALOE VERA LEAF; ROSEMARY; MALTODEXTRIN; CERAMIDE NP; .BETA.-SITOSTEROL; CHLORPHENESIN; TOCOPHEROL; POTASSIUM SORBATE; SODIUM BENZOATE

G&H Protect Hand Sanitizer

Active Ingredient

Ethyl alcohol 65.6%

Purpose

Antiseptic

Uses

Hand sanitizer to help reduce bacteria on the skin that potentially can cause disease. For use when soap and water are not available.

Warnings

For external use only. Flammable. Keep away from heat or flame.

Do not use

- In children less than 2 years of age.
- On open skin wounds.

When using this product

keep out of eyes, ears, and mouth. In case of contact with eyes, rinse eyes thoroughly with water.

Stop use and ask a doctor

if irritation or rash occurs. These may be signs of a serious condition.

Keep out of reach of children.

If swallowed, get medical help or contact a Poison Control Center right away

Directions

- Place enough product on hands to cover all surfaces. Rub thoroughly into hands for at least 30 seconds. Allow to dry.
- Supervise children under 6 years of age when using this product to avoid swallowing.

Other information

- Store between 15-30°C (59-86°F)
- Avoid freezing and excessive heat above 40°C (104°F).

Inactive ingredients

Water, Glycerin, Fragrance, Carbomer, Tetrahydroxypropyl Ethylenediamine, Propylene Glycol, Butylene Glycol, Lecithin, Centella Asiatica Extract, Camellia Sinensis Leaf Extract, Phenoxyethanol, Aloe Barbadensis Leaf Juice, Rosmarinus Officinalis (Rosemary) Leaf Extract, Maltodextrin, Ceramide NP, Beta-Sitosterol, Chlorphenesin, Tocopherol, Potassium Sorbate, Sodium Benzoate

Questions?

USA: 1-800-253-6500